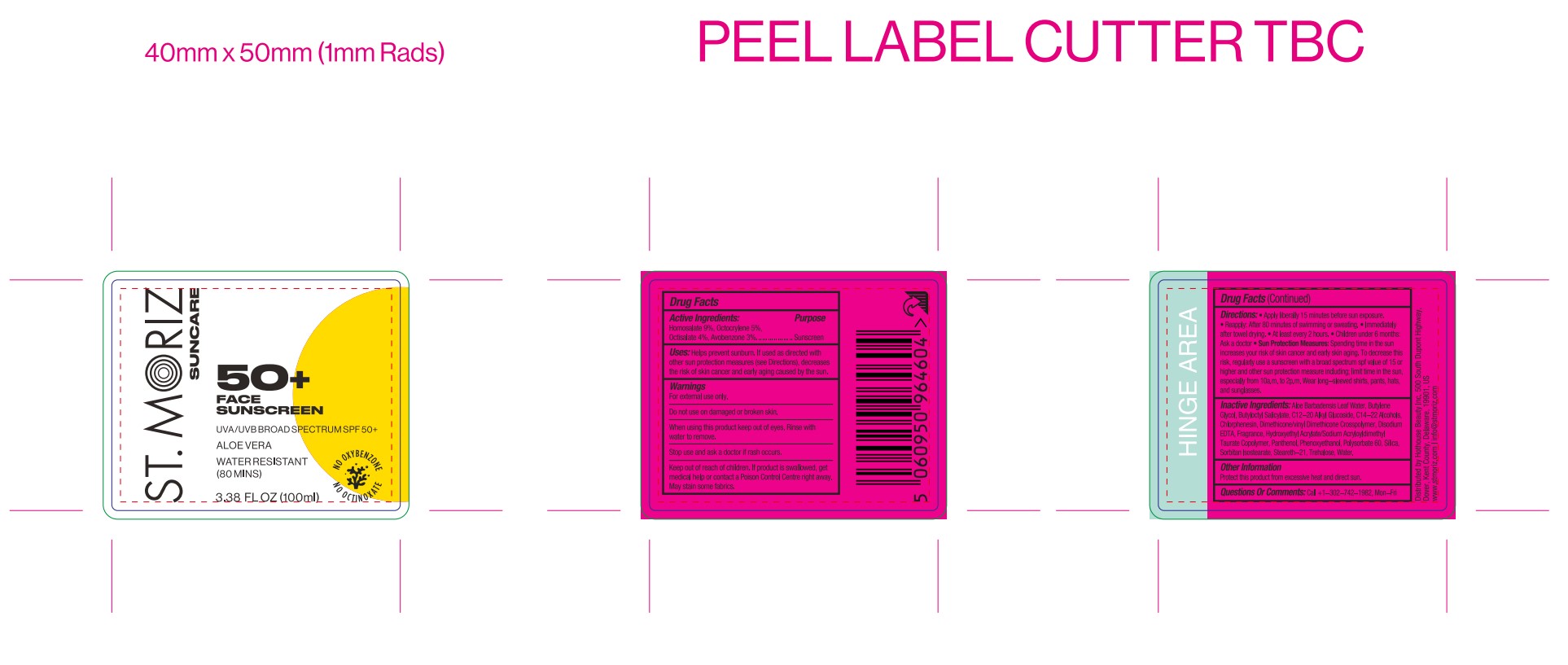 DRUG LABEL: St Moriz suncare face sunscreen spf50
NDC: 82723-016 | Form: LOTION
Manufacturer: Aopline Health Industry Technology (Guangzhou) Co., Ltd.
Category: otc | Type: HUMAN OTC DRUG LABEL
Date: 20250127

ACTIVE INGREDIENTS: OCTOCRYLENE 9 mg/180 mL; HOMOSALATE 16.2 mg/180 mL; AVOBENZONE 5.4 mg/180 mL; OCTISALATE 7.2 mg/180 mL
INACTIVE INGREDIENTS: SILICA; STEARETH-21; SORBITAN ISOSTEARATE; BUTYLENE GLYCOL; ALOE BARBADENSIS LEAF WATER; C14-22 ALCOHOLS; WATER; BUTYLOCTYL SALICYLATE; HYDROXYETHYL ACRYLATE/SODIUM ACRYLOYLDIMETHYL TAURATE COPOLYMER (45000 MPA.S AT 1%); POLYSORBATE 60; DIMETHICONE/VINYL DIMETHICONE CROSSPOLYMER (SOFT PARTICLE); PHENOXYETHANOL; CHLORPHENESIN; EDETATE DISODIUM; PANTHENOL; TREHALOSE; C12-20 ALKYL GLUCOSIDE

Active Ingredients

OCTOCRYLENE
OCTISALATE
AVOBENZONE
HOMOSALATE

Purpose

Sunscreen

Uses

Uses: Helps prevent sunburn.

Warnings

For external use only .
Do not use on broken or damaged skin .
Stop use and ask a doctor if rash occurs
When using this product keep out of eyes . Rinse with water to remove .
Keep out of reach of children . If product is swallowed , get medical help or contact a
Poison Control Center right away .

Directions

Directions : Apply liberally 15 minutes before sun or water exposure. Works best on
moisturized skin.
Reapply:
After 80 minutes of swimming or sweating.
Immediately after towel drying.
At least every 2 hours.
Children under 6 months: Ask a doctor.

Inactive Ingredients

BUTYLENE GLYCOL
WATER
C14-22 ALCOHOLS
C12-20 ALKYL GLUCOSIDE
BUTYLOCTYL SALICYLATE
STEARETH-21
HYDROXYETHYL ACRYLATE/SODIUM ACRYLOYLDIMETHYL TAURATE COPOLYMER
POLYSORBATE 60
SORBITAN ISOSTEARATE
TREHALOSE
DIMETHICONE/VINYL DIMETHICONE CROSSPOLYMER
SILICA
PHENOXYETHANOL
CHLORPHENESIN
FRAGRANCE
DISODIUM EDTA
PANTHENOL
ALOE BARBADENSIS LEAF WATER

Keep out of reach of children . If product is swallowed , get medical help or contact a
Poison Control Center right away

Stop use

Stop use and ask a doctor if rash occurs
When using this product keep out of eyes . Rinse with water to remove .
When using this product keep out of eyes . Rinse with water to remove .
Keep out of reach of children . If product is swallowed , get medical help or contact a
Poison Control Center right away .

Do not use on broken or damaged skin .
Stop use and ask a doctor if rash occurs

INDICATIONS AND USAGE

Directions : Apply liberally 15 minutes before sun or water exposure. Works best on
moisturized skin.
Reapply:
After 80 minutes of swimming or sweating.
Immediately after towel drying.
At least every 2 hours.
Children under 6 months: Ask a doctor.